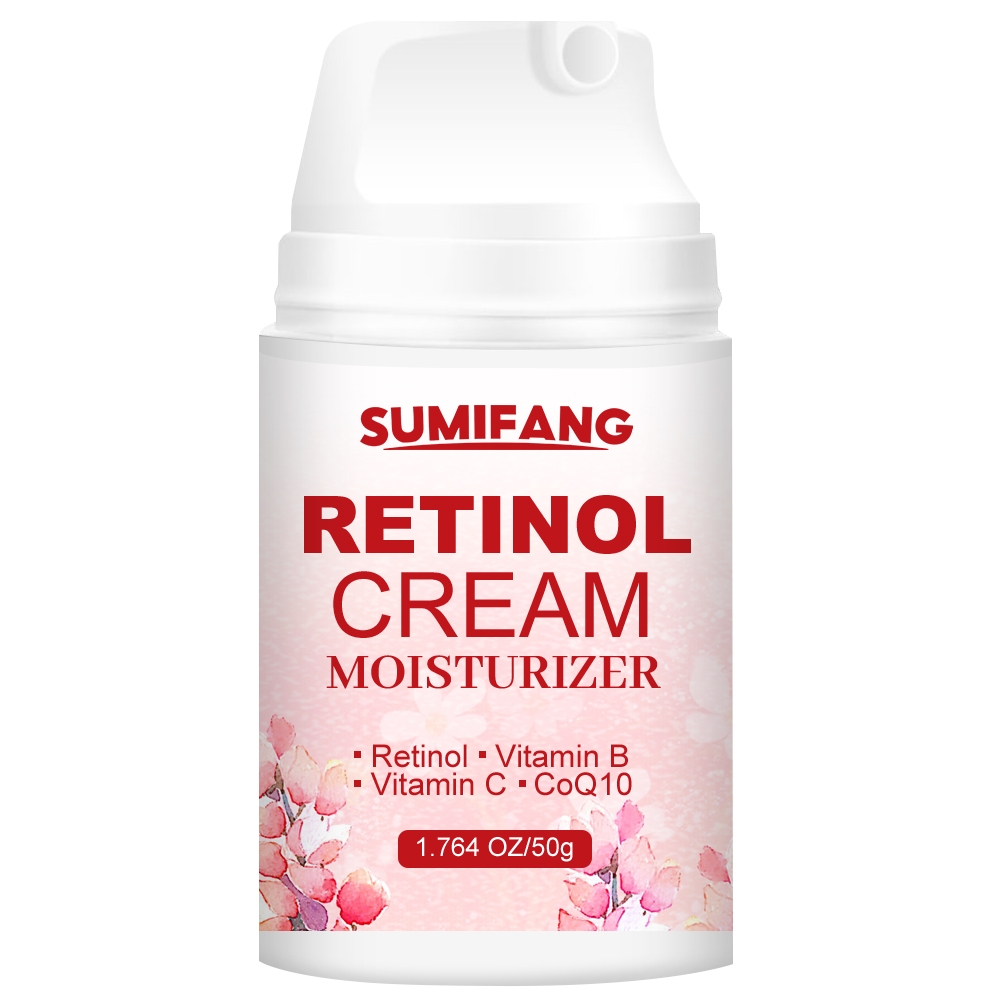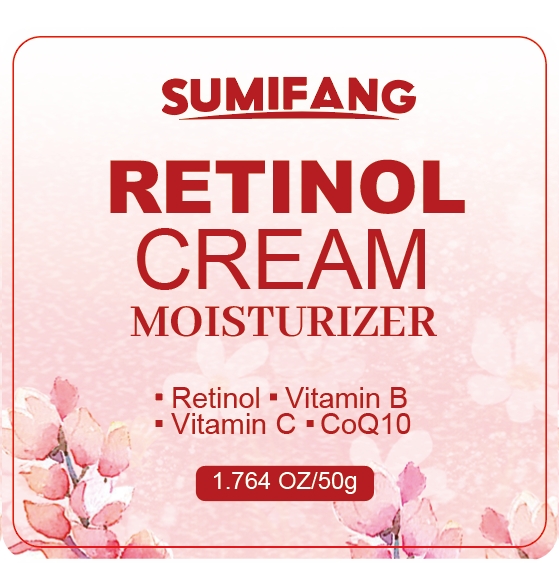 DRUG LABEL: Retionl Cream
NDC: 84025-157 | Form: CREAM
Manufacturer: Guangzhou Yanxi Biotechnology Co.. Ltd
Category: otc | Type: HUMAN OTC DRUG LABEL
Date: 20240817

ACTIVE INGREDIENTS: GLYCERIN 3 mg/50 g; HYALURONIC ACID 5 mg/50 g
INACTIVE INGREDIENTS: WATER

DOSAGE AND ADMINISTRATION

Facial cream for moisturizing facial skin

WARNINGS

keep out of children

INACTIVE INGREDIENT

Aqua

INDICATIONS AND USAGE

For daily skin care

Keep out of children

PURPOSE

Moisturizes and cares for facial skin and keeps skin dry